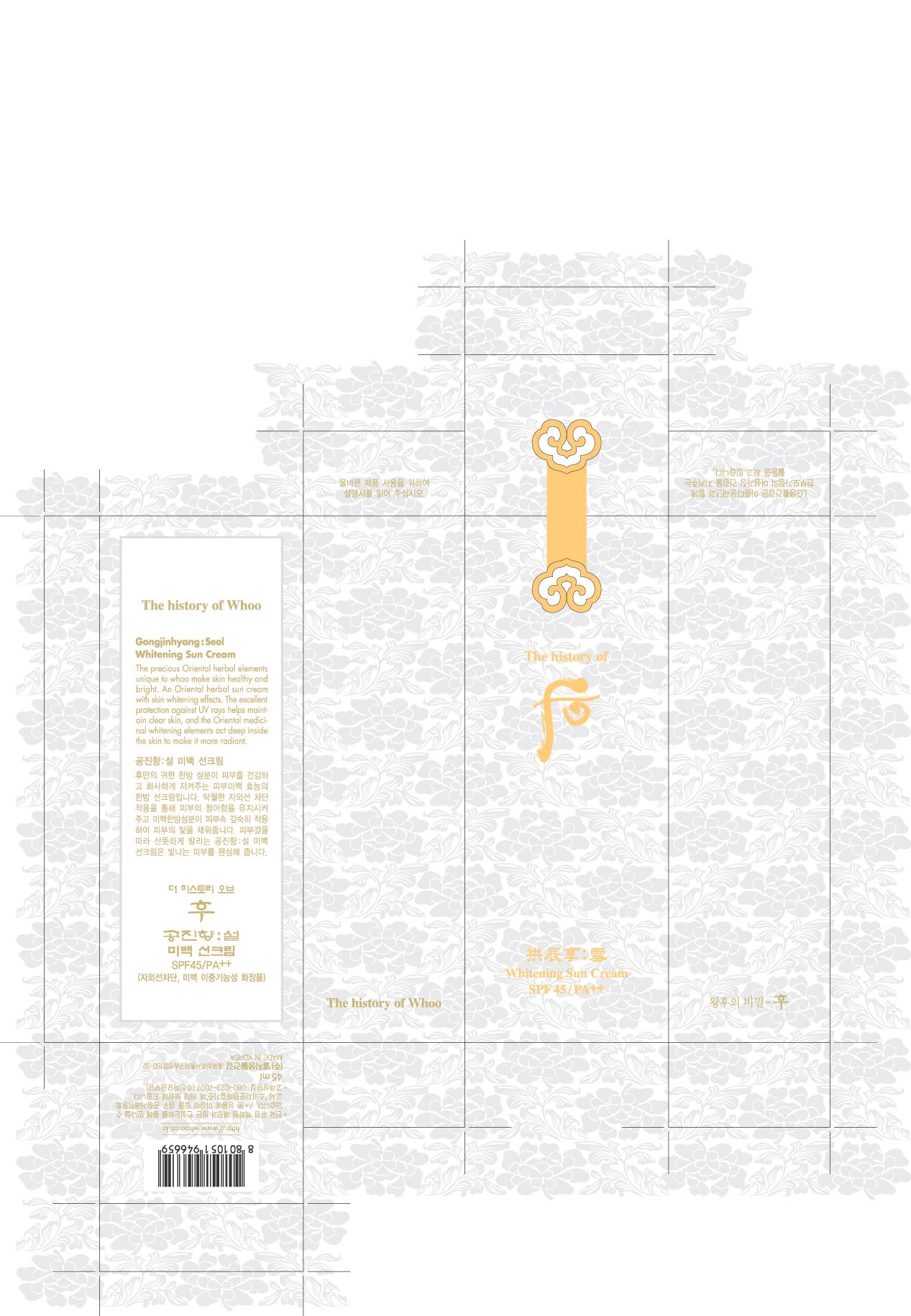 DRUG LABEL: THE HISTORY OF WHOO GONGJINHYANG SEOL WHITENING SUN
NDC: 53208-525 | Form: CREAM
Manufacturer: LG Household and Healthcare, Inc.
Category: otc | Type: HUMAN OTC DRUG LABEL
Date: 20110422

ACTIVE INGREDIENTS: ZINC OXIDE 6.117 mL/100 mL; ENSULIZOLE 3.9 mL/100 mL; TITANIUM DIOXIDE 2.48 mL/100 mL; ATRACTYLODES JAPONICA ROOT OIL 0.05 mL/100 mL; POLYSILICONE-15 3 mL/100 mL
INACTIVE INGREDIENTS: WATER; PHENYL TRIMETHICONE; DIMETHICONE; DIPROPYLENE GLYCOL; BUTYLENE GLYCOL; TROMETHAMINE; CYCLOMETHICONE 5; CYCLOMETHICONE 6; GLYCERIN; ZINC STEARATE; 1,2-HEXANEDIOL; HECTORITE; MAGNESIUM SULFATE, UNSPECIFIED; STEARIC ACID; DISTEARYLDIMONIUM CHLORIDE; ACETATE ION; MICA; ANGELICA ACUTILOBA ROOT; CORNUS OFFICINALIS FRUIT; FERRIC OXIDE RED; TRIETHOXYCAPRYLYLSILANE; DIOSMETIN

DRUG FACTS

ACTIVE INGREDIENT

ZINC OXIDE 6.117%
ENSULIZOLE 3.9%
POLYSILICONE-15 3%
TITANIUM DIOXIDE 2.48%
ATRACTYLODES JAPONICA ROOT OIL 0.05%

WARNINGS AND PRECAUTIONS

For external use only

Keep out of reach of children. Is swallowed, get medical help or contact a Poison Control Center right away.

WHEN USING

Keep out of eyes. Rinse with water to remove.

Stop use if a rash or irritation develops and lasts.